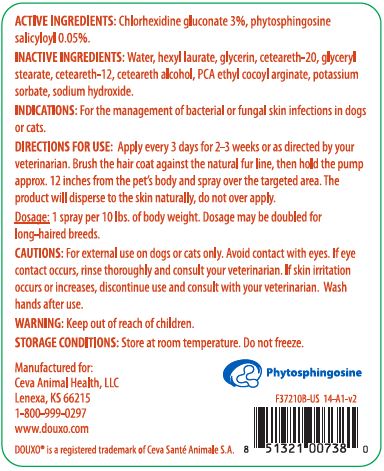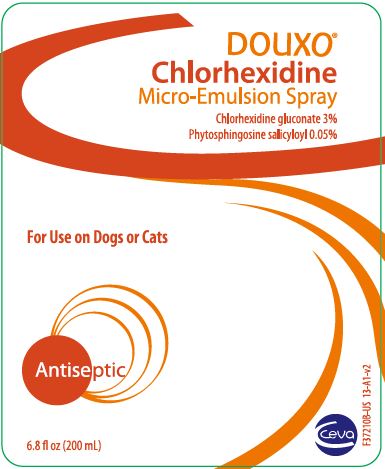 DRUG LABEL: DOUXO CHLORHEXIDINE
NDC: 13744-120 | Form: SPRAY
Manufacturer: Ceva Sante Animale
Category: animal | Type: OTC ANIMAL DRUG LABEL
Date: 20220623

ACTIVE INGREDIENTS: CHLORHEXIDINE GLUCONATE 30 mg/1 mL; SALICYLOYL PHYTOSPHINGOSINE .5 mg/1 mL
INACTIVE INGREDIENTS: WATER; HEXYL LAURATE; GLYCERIN; CETOSTEARYL ALCOHOL; POLYOXYL 20 CETOSTEARYL ETHER; CETEARETH-12; GLYCERYL STEARATE SE; PYRROLIDONE CARBOXYLIC ACID ETHYL COCOYL ARGINATE; POTASSIUM SORBATE; SODIUM HYDROXIDE

DESCRIPTION

DOUXO®

Chlorhexidine

Micro-emulsion Spray

ACTIVE INGREDIENTS: Chlorhexidine gluconate 3% phytosphingosine salicyloyl 0.05%.

INACTIVE INGREDIENTS: Water, hexyl laurate, glycerin, cetearyl alcohol, ceteareth-20, ceteareth-12, glyceryl stearate, PCA ethyl cocoyl arginate, potassium sorbate, sodium hydroxide.

INDICATIONS AND USAGE

INDICATIONS: For the management of bacterial and fungal skin infections in dogs or cats.

DIRECTIONS FOR USE: Apply every 3 days for 2 to 3 weeks or as recomended by your veterinarian. Brush the hair coat against the natural fur line, then hold the pump approx. 12 inches from the pet's body and spray over the targeted area. The product will disperse to the skin naturally, do not over apply.

Dosage: 1 spray per 10 lbs. of bodyweight. Dosage may be doubled for long-haired breeds.

PRECAUTIONS

CAUTIONS: For external use on dogs or cats only. Avoid contact with the eyes. If eye contact occurs, rinse thoroughly and consult your veterinarian. If irritation occurs or increases, discontinue use and consult with your veterinarian. Wash hands after use.

WARNING: Keep out of the reach of children.

STORAGE CONDITIONS: Store at room temperature. Do not freeze.

Manufactured for:

Ceva Animal Health, LLC

Lenexa, KS 66215

1-800-999-0297

www.douxo.com

Douxo® is a registered trademark of Ceva Santé Animale S.A.

PRINCIPAL DISPLAY PANEL - 200 mL (6.8 OUNCE) Bottle

DOUXO®

Chlorhexidine

Micro-Emulsion Spray

Chlorhexidine gluconate 3%

Phytosphingosine salicloyl 0.05%

Antiseptic

Phytosphingosine

200 mL (6.8 fl. oz.)

Ceva